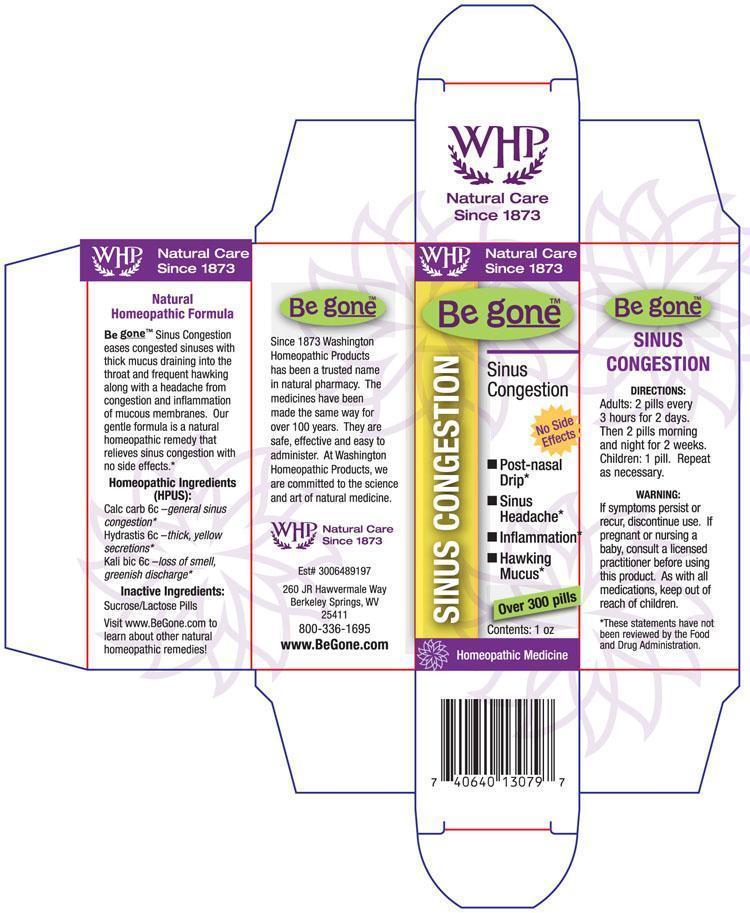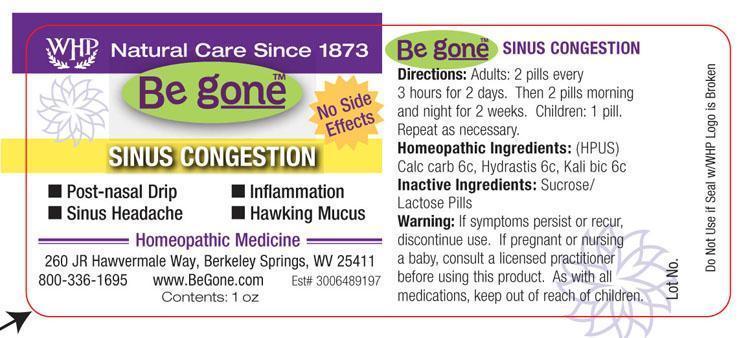 DRUG LABEL: Be gone Sinus Congestion
NDC: 68428-730 | Form: PELLET
Manufacturer: Washington Homeopathic Products
Category: homeopathic | Type: HUMAN OTC DRUG LABEL
Date: 20191223

ACTIVE INGREDIENTS: OYSTER SHELL CALCIUM CARBONATE, CRUDE 6 [hp_C]/28 g; GOLDENSEAL 6 [hp_C]/28 g; POTASSIUM DICHROMATE 6 [hp_C]/28 g
INACTIVE INGREDIENTS: SUCROSE; LACTOSE

DRUG FACTS

ACTIVE INGREDIENTS

CALC CARB 6C

HYDRASTIS 6C

KALI BIC 6C

USES

To relieve the symptoms of congested sinuses and headaches relating to congested sinuses.

KEEP OUT OF REACH OF CHILDREN

As with all medications, keep out of reach of children.

INDICATIONS

CALC CARB - OVERWORK

HYDRASTIS - SINUSES

KALI BIC - SINUSES

STOP USE AND ASK DOCTOR

If symptoms persist or recur, discontinue use. If pregnant or nursing a baby, consult a licensed practitioner before using this product.

DIRECTIONS

Adults 2 pellets every 3 hours for 2 days. Then 2 pellets morning and night for 2 weeks.

Children: 1 pellet. Repeat as necessary.

INACTIVE INGREDIENTS

Sucrose/Lactose

PRINCIPAL DISPLAY PANEL

Be g oneTM Sinus Congesion label

Be g oneTM Sinus Congestion box